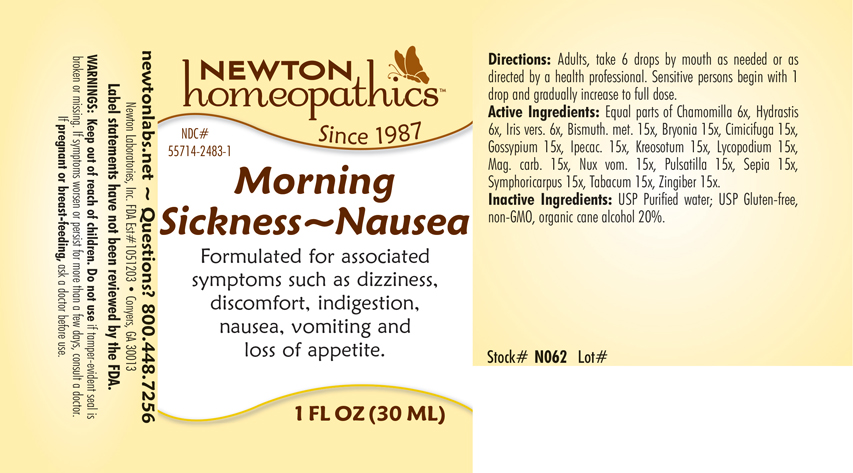 DRUG LABEL: Morning Sickness-Nausea
NDC: 55714-2483 | Form: LIQUID
Manufacturer: Newton Laboratories, Inc.
Category: homeopathic | Type: HUMAN OTC DRUG LABEL
Date: 20250207

ACTIVE INGREDIENTS: IRIS VERSICOLOR ROOT 6 [hp_X]/1 mL; BISMUTH 15 [hp_X]/1 mL; BRYONIA ALBA ROOT 15 [hp_X]/1 mL; BLACK COHOSH 15 [hp_X]/1 mL; GOSSYPIUM HERBACEUM ROOT BARK 15 [hp_X]/1 mL; IPECAC 15 [hp_X]/1 mL; WOOD CREOSOTE 15 [hp_X]/1 mL; LYCOPODIUM CLAVATUM SPORE 15 [hp_X]/1 mL; MAGNESIUM CARBONATE 15 [hp_X]/1 mL; STRYCHNOS NUX-VOMICA SEED 15 [hp_X]/1 mL; MATRICARIA CHAMOMILLA 6 [hp_X]/1 mL; GINGER 15 [hp_X]/1 mL; SEPIA OFFICINALIS JUICE 15 [hp_X]/1 mL; SYMPHORICARPOS ALBUS FRUIT 15 [hp_X]/1 mL; TOBACCO LEAF 15 [hp_X]/1 mL; GOLDENSEAL 6 [hp_X]/1 mL; ANEMONE PULSATILLA 15 [hp_X]/1 mL
INACTIVE INGREDIENTS: WATER; ALCOHOL

Morning 2483L

INDICATIONS & USAGE SECTION

Formulated for associated symptoms such as dizziness, discomfort, indigestion, nausea, vomiting and loss of appetite.

DOSAGE & ADMINISTRATION SECTION

Directions: Adults, take 6 drops by mouth as needed or as directed by a health professional. Sensitive persons begin with 1 drop and gradually increase to full dose.

OTC - ACTIVE INGREDIENT SECTION

Equal parts of Chamomilla 6x, Hydrastis canadensis 6x, Iris versicolor 6x, Bismuthum metallicum 15x, Bryonia 15x, Cimicifuga racemosa 15x, Gossypium herbaceum 15x, Ipecacuanha 15x, Kreosotum 15x, Lycopodium clavatum 15x, Magnesia carbonica 15x, Nux vomica 15x, Pulsatilla 15x, Sepia 15x, Symphoricarpus racemosus 15x, Tabacum 15x, Zingiber officinale 15x.

OTC - PURPOSE SECTION

Formulated for associated symptoms such as irregularity, cramping, bloating, headache, cravings, emotional upsets and mood swings.

INACTIVE INGREDIENT SECTION

Inactive Ingredients: USP Purified Water; USP Gluten-free, non-GMO, organic cane alcohol 20%.

QUESTIONS SECTION

newtonlabs.net – Questions? 800.448.7256

Newton Laboratories, Inc. FDA Est # 1051203 - Conyers, GA 30013

WARNINGS SECTION

WARNINGS: Keep out of reach of children. Do not use if tamper-evident seal is broken or missing. If symptoms worsen or persist for more than a few days, consult a doctor. If pregnant or breast-feeding, ask a doctor before use.

OTC - PREGNANCY OR BREAST FEEDING SECTION

If pregnant or breast-feeding, ask a doctor before use.

OTC - KEEP OUT OF REACH OF CHILDREN SECTION

Keep out of reach of children.